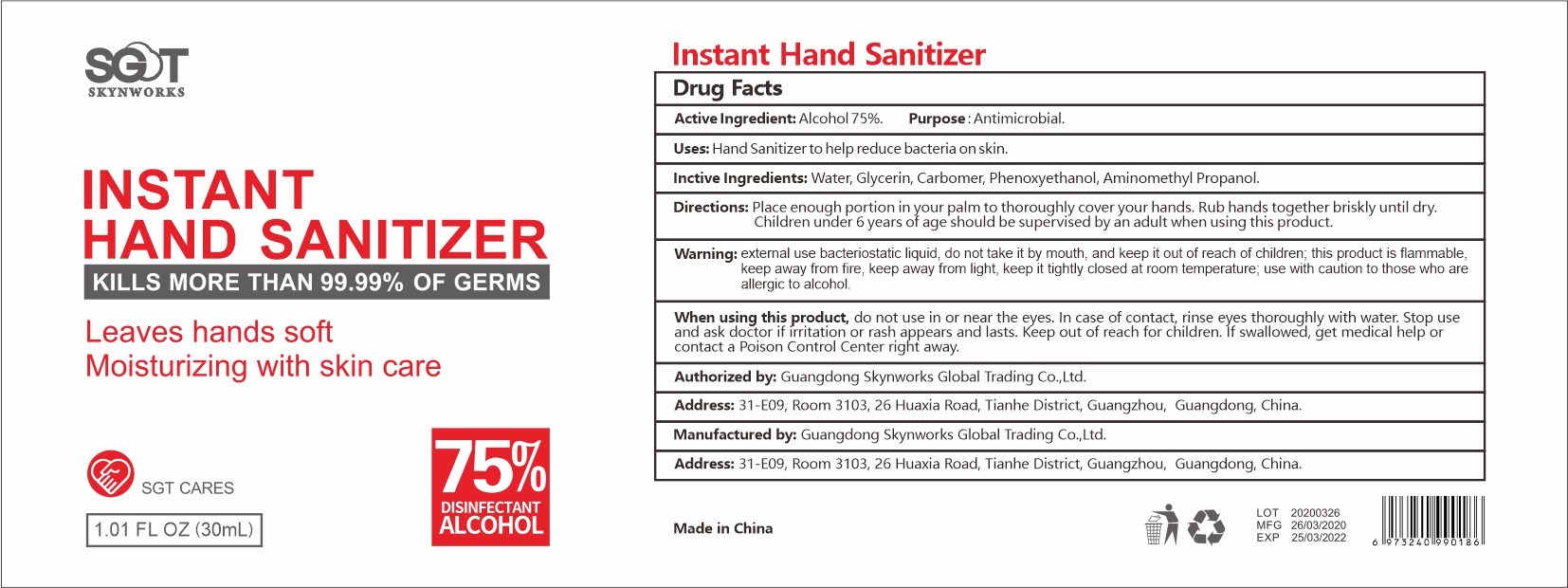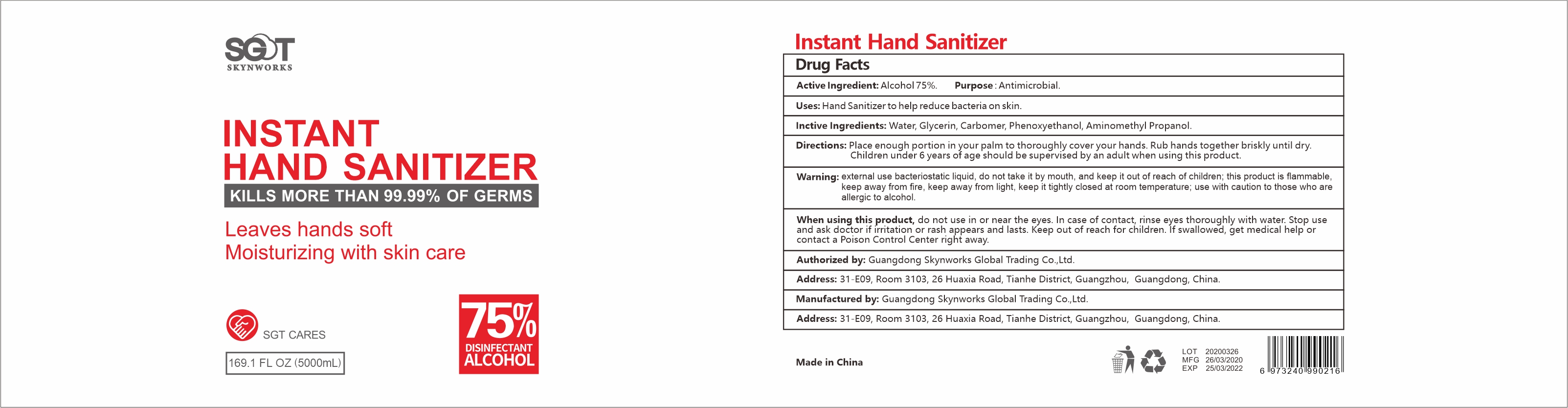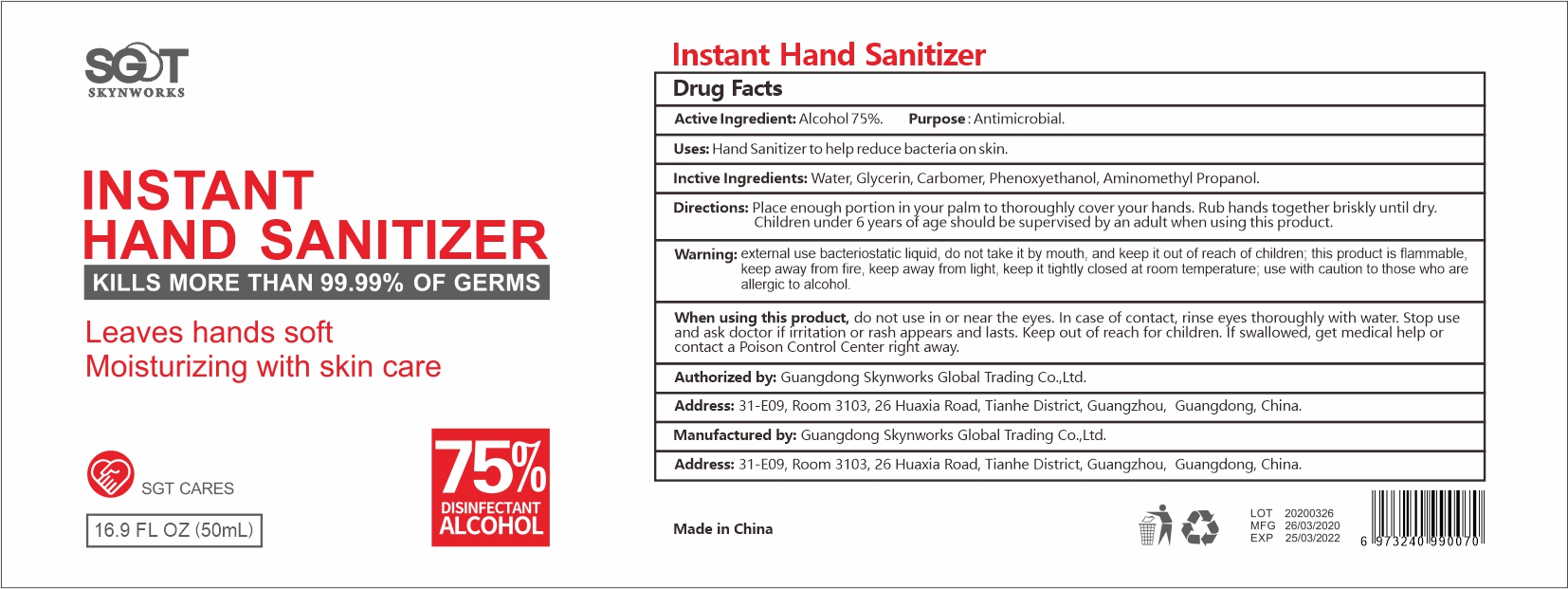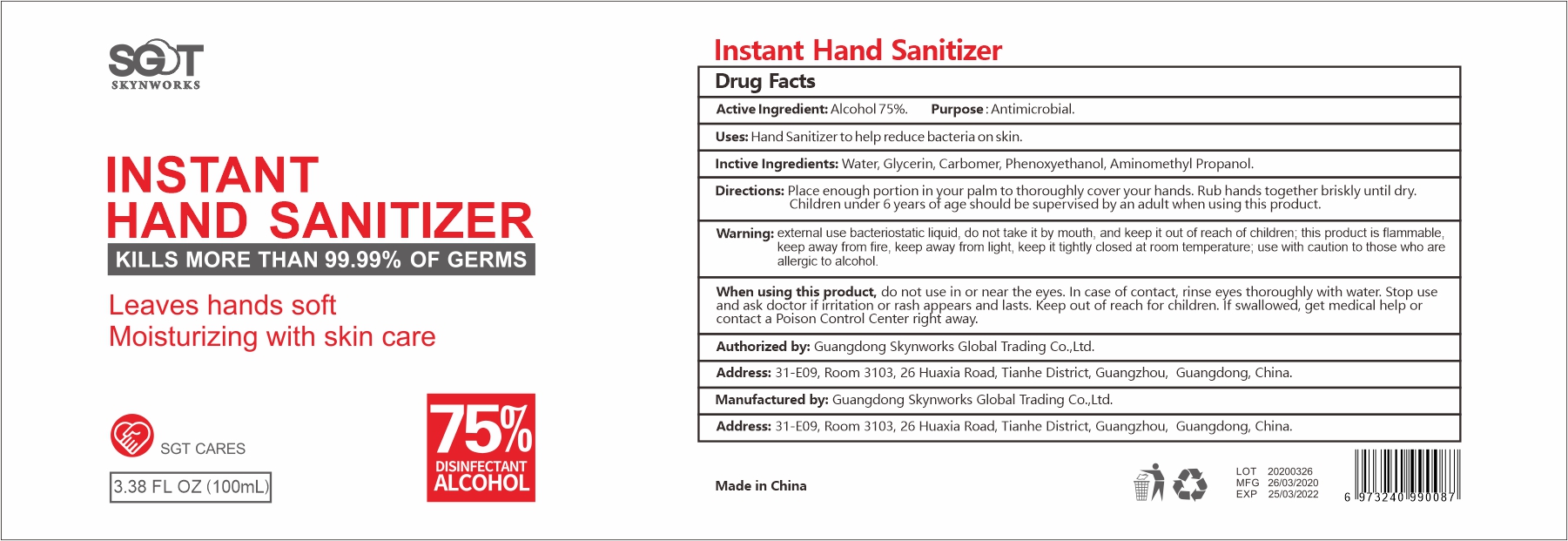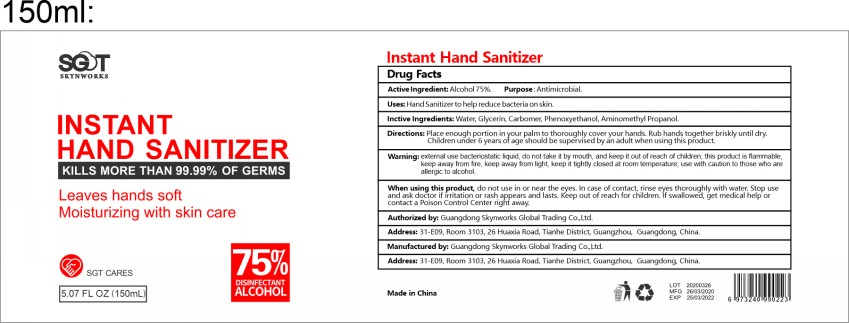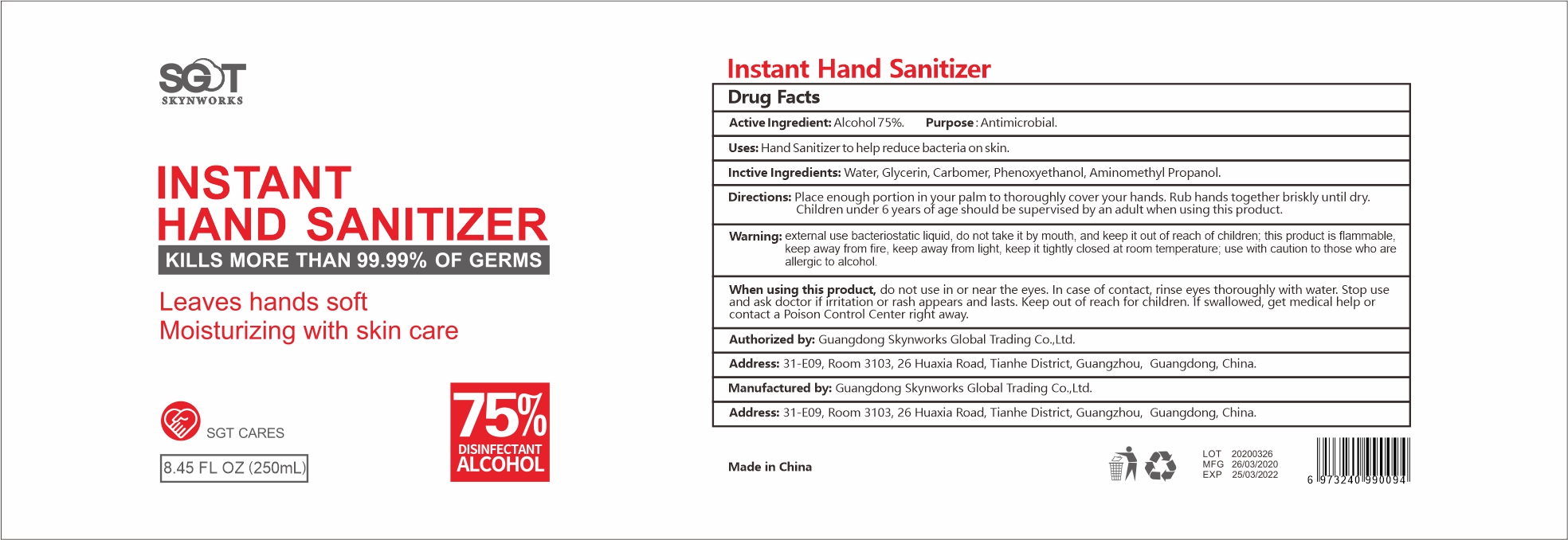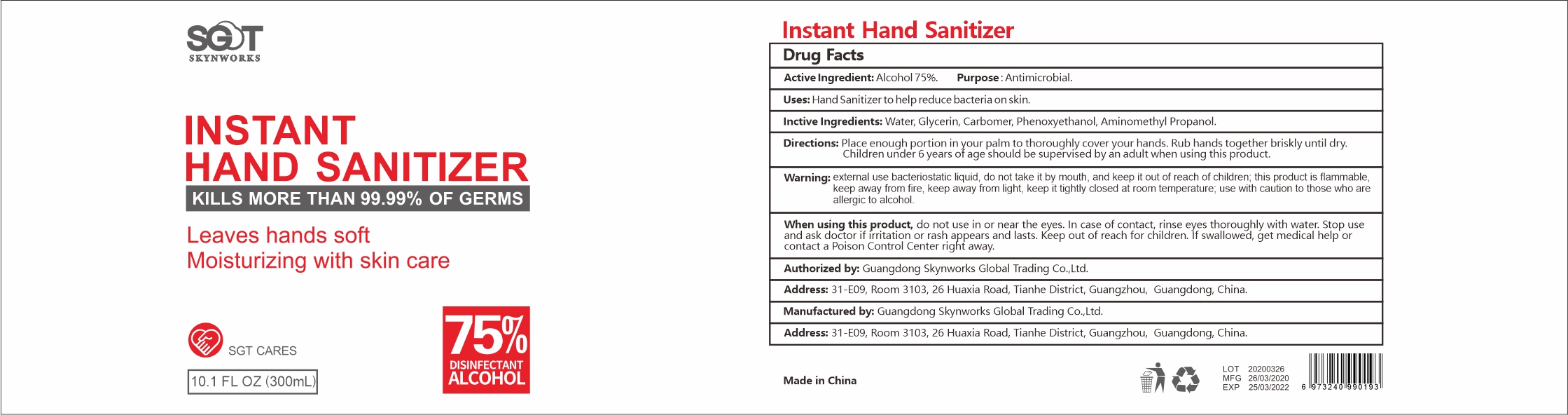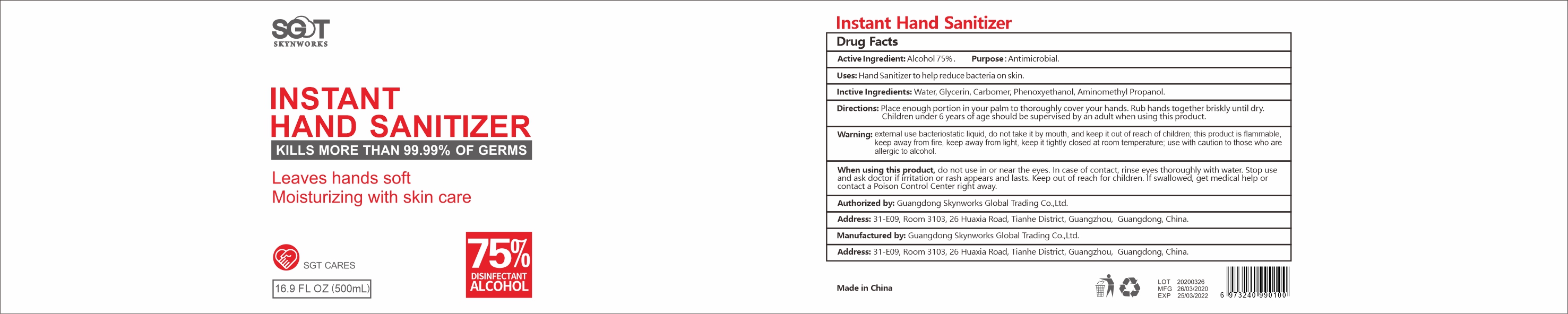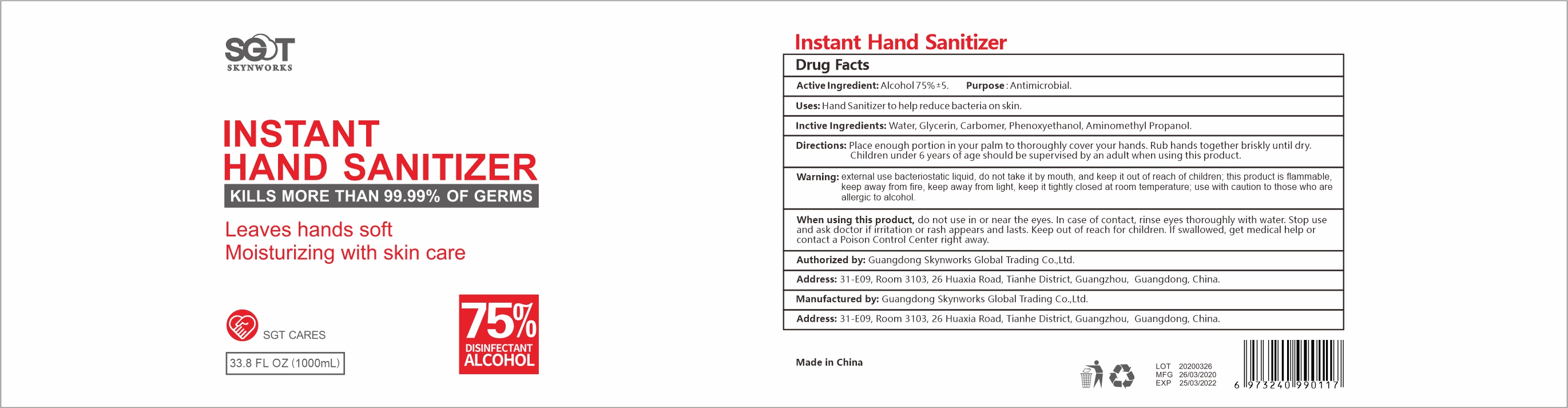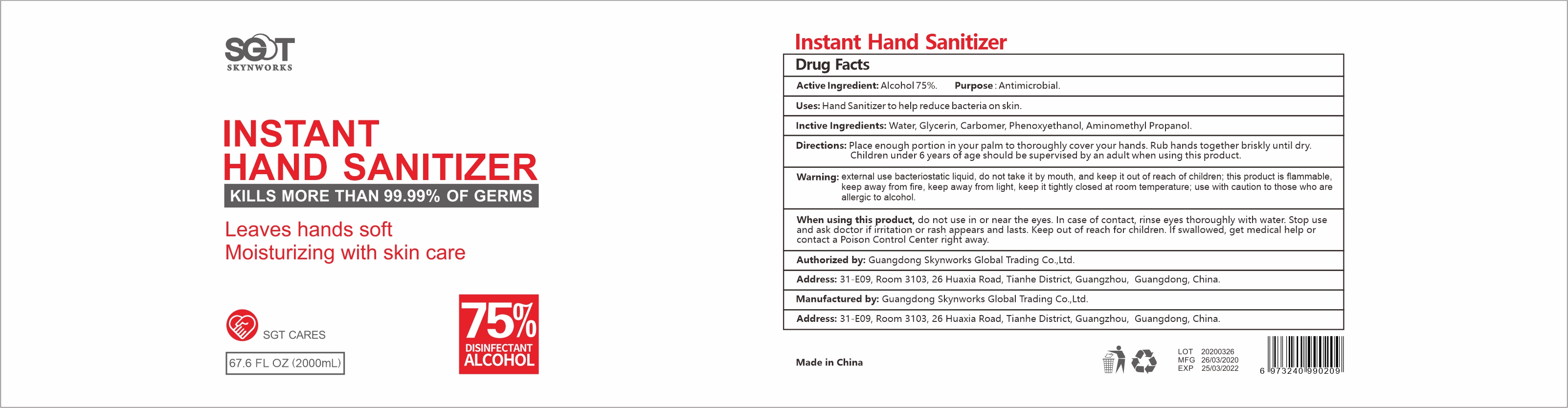 DRUG LABEL: Instant Hand Sanitizer
NDC: 75117-001 | Form: GEL
Manufacturer: Guangdong Skynworks Global Trading Co., Ltd.
Category: otc | Type: HUMAN OTC DRUG LABEL
Date: 20200502

ACTIVE INGREDIENTS: ALCOHOL 75 mL/100 mL
INACTIVE INGREDIENTS: GLYCERIN; WATER; CARBOMER HOMOPOLYMER, UNSPECIFIED TYPE; AMINOMETHYLPROPANOL; PHENOXYETHANOL

Instant Hand Sanitizer

Active Ingredient

Alcohol 75%

Purpose

Antimicrobial

Uses

Hand Sanitizer to help reduce bacteria on skin.

Warning

external use bacteriostatic liquid, do not take it by mouth, and keep it out of reach of children;this product is flammable,

keep away from fire, keep away from light, keep it tightly closed at room temperature; use with caution to those who are

allergic to alcohol.

When using this product

do not use in or near the eyes.In case of contact, rinse eyes thoroughly with water.Stop use and ask a doctor if irritation or rash appears and lasts.Keep out of reach for children.If swallowed,get medical help or contact a Poison Control Center right away.

Directions

Place enough portion in your palm to thoroughly cover your hands.Rub hands together briskly until dry.

Children under 6 years of age should be supervised by an adult when using this product.

Inactive Ingredients

Water,Glycerin, Carbomer, Phenoxyethanol,Aminomethyl Propanol.